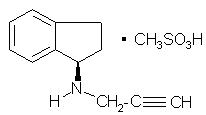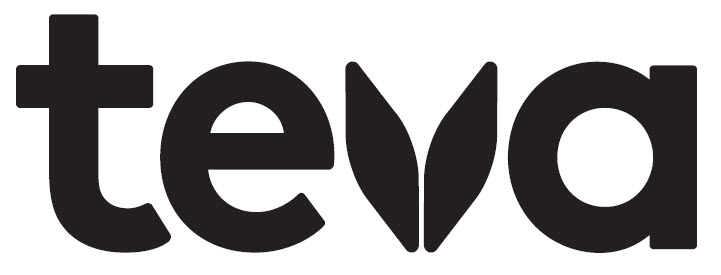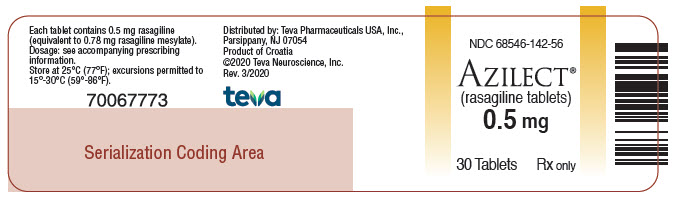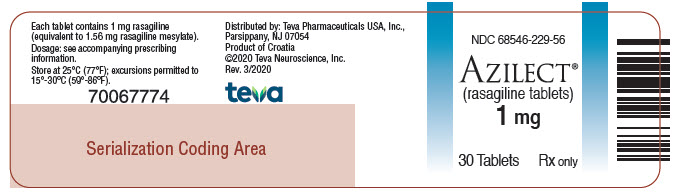 DRUG LABEL: Azilect
NDC: 68546-229 | Form: TABLET
Manufacturer: Teva Neuroscience, Inc.
Category: prescription | Type: HUMAN PRESCRIPTION DRUG LABEL
Date: 20200630

ACTIVE INGREDIENTS: RASAGILINE MESYLATE 1 mg/1 1
INACTIVE INGREDIENTS: MANNITOL; STARCH, CORN; SILICON DIOXIDE; STEARIC ACID; TALC

HIGHLIGHTS OF PRESCRIBING INFORMATION

These highlights do not include all the information needed to use AZILECT® safely and effectively. See full prescribing information for AZILECT.
AZILECT (rasagiline) Tablets for Oral Use
Initial U.S. Approval: 2006

1 INDICATIONS AND USAGE

AZILECT, a monoamine oxidase (MAO)-B inhibitor (MAOI), is indicated for the treatment of Parkinson’s disease (1)

2 DOSAGE AND ADMINISTRATION

- Monotherapy: AZILECT 1 mg once daily (2.1)
- As adjunct without levodopa: AZILECT 1 mg once daily (2.1)
- As adjunct to levodopa: AZILECT 0.5 mg once daily. Increase dose to 1 mg daily as needed for sufficient clinical response (2.1)
- Patients taking ciprofloxacin or other CYP1A2 inhibitors: AZILECT 0.5 mg once daily (2.2, 5.4)
- Patients with mild hepatic impairment: AZILECT 0.5 mg once daily. AZILECT should not be used in patients with moderate or severe hepatic impairment (2.3, 5.5)

3 DOSAGE FORMS AND STRENGTHS

- AZILECT 0.5 mg tablets (3)
- AZILECT 1 mg tablets (3)

4 CONTRAINDICATIONS

Concomitant use of meperidine, tramadol, methadone, propoxyphene dextromethorphan, St. John’s wort, cyclobenzaprine, or another (selective or non-selective) MAO inhibitor (4)

5 WARNINGS AND PRECAUTIONS

- May cause hypertension (including severe hypertensive syndromes) at recommended doses (5.1)
- May cause serotonin syndrome when used with antidepressants (5.2)
- May cause falling asleep during activities of daily living, daytime drowsiness, and somnolence (5.3)
- May cause hypotension, especially orthostatic (5.6)
- May cause or exacerbate dyskinesia. Decreasing the levodopa dose may lessen or eliminate this side effect (5.7)
- May cause hallucinations and psychotic-like behavior (5.8)
- May cause impulse control/compulsive behaviors (5.9)
- May cause withdrawal-emergent hyperpyrexia and confusion (5.10)

6 ADVERSE REACTIONS

Most common adverse reactions (incidence 3% or greater than placebo):

- AZILECT monotherapy: flu syndrome, arthralgia, depression, dyspepsia (6.1)
- AZILECT used as adjunct without levodopa: peripheral edema, fall, arthralgia, cough, and insomnia (6.1)
- AZILECT used as adjunct to levodopa: dyskinesia, accidental injury, weight loss, postural hypotension, vomiting, anorexia, arthralgia, abdominal pain, nausea, constipation, dry mouth, rash, abnormal dreams, fall, and tenosynovitis (6.1)

To report SUSPECTED ADVERSE REACTIONS, contact Teva Pharmaceuticals at 1-888-483-8279 or FDA at 1-800-FDA-1088 or www.fda.gov/medwatch.

7 DRUG INTERACTIONS

- Meperidine: Risk of serotonin syndrome (4, 7.1)
- Dextromethorphan: Risk of psychosis or bizarre behavior (4, 7.2)
- MAO inhibitors: Risk of non-selective MAO inhibition and hypertensive crisis (4, 7.3)

8 USE IN SPECIFIC POPULATIONS

- Pregnancy: Based on animal data, may cause fetal harm. (8.1)

FULL PRESCRIBING INFORMATION

1 INDICATIONS AND USAGE

AZILECT (rasagiline tablets) is indicated for the treatment of Parkinson’s disease (PD).

2 DOSAGE AND ADMINISTRATION

2.1 General Dosing Recommendations

When AZILECT is prescribed as monotherapy or as adjunct therapy in patients not taking levodopa, patients may start AZILECT at the recommended dose of 1 mg administered orally once daily.

In patients taking levodopa, with or without other PD drugs (e.g., dopamine agonist, amantadine, anticholinergics), the recommended initial dose of AZILECT is 0.5 mg once daily. If the patient tolerates the daily 0.5 mg dose, but a sufficient clinical response is not achieved, the dose may be increased to 1 mg once daily. When AZILECT is used in combination with levodopa, a reduction of the levodopa dose may be considered, based upon individual response.

The recommended doses of AZILECT should not be exceeded because of risk of hypertension [see Warnings and Precautions (5.1)].

2.2 Patients Taking Ciprofloxacin or Other CYP1A2 Inhibitors

Patients taking concomitant ciprofloxacin or other CYP1A2 inhibitors should not exceed a dose of AZILECT 0.5 mg once daily [see Warnings and Precautions (5.4), Drug Interactions (7.6), and Clinical Pharmacology (12.3)].

2.3 Patients with Hepatic Impairment

Patients with mild hepatic impairment should not exceed a dose of AZILECT 0.5 mg once daily. AZILECT should not be used in patients with moderate or severe hepatic impairment [see Warnings and Precautions (5.5), Use in Specific Populations (8.6), and Clinical Pharmacology (12.3)].

3 DOSAGE FORMS AND STRENGTHS

AZILECT 0.5 mg Tablets: White to off-white, round, flat, beveled tablets, debossed with “GIL 0.5” on one side and plain on the other side.

AZILECT 1 mg Tablets: White to off-white, round, flat, beveled tablets, debossed with “GIL 1” on one side and plain on the other side.

4 CONTRAINDICATIONS

AZILECT is contraindicated for use with meperidine, tramadol, methadone, propoxyphene, and MAO inhibitors (MAOIs), including other selective MAO-B inhibitors, because of risk of serotonin syndrome [see Warnings and Precautions (5.2)]. At least 14 days should elapse between discontinuation of AZILECT and initiation of treatment with these medications.

AZILECT is contraindicated for use with St. John’s wort and with cyclobenzaprine.

AZILECT is contraindicated for use with dextromethorphan because of risk of episode of psychosis or bizarre behavior.

5 WARNINGS AND PRECAUTIONS

5.1 Hypertension

Exacerbation of hypertension may occur during treatment with AZILECT. Medication adjustment may be necessary if elevation of blood pressure is sustained. Monitor patients for new onset hypertension or hypertension that is not adequately controlled after starting AZILECT.

In Study 3, AZILECT (1 mg/day) given in conjunction with levodopa, produced an increased incidence of significant blood pressure elevation (systolic > 180 or diastolic > 100 mm Hg) of 4% compared to 3% for placebo [see Adverse Reactions (6.1)].

When used as an adjunct to levodopa (Studies 3 and 4), the risk for developing post-treatment high blood pressure (e.g., systolic > 180 or diastolic >100 mm Hg) combined with a significant increase from baseline (e.g., systolic > 30 or diastolic > 20 mm Hg) was higher for AZILECT (2%) compared to placebo (1%).

Dietary tyramine restriction is not required during treatment with recommended doses of AZILECT. However, certain foods that may contain very high amounts (i.e., more than 150 mg) of tyramine that could potentially cause severe hypertension because of tyramine interaction (including various clinical syndromes referred to as hypertensive urgency, crisis, or emergency) in patients taking AZILECT, even at the recommended doses, due to increased sensitivity to tyramine. Patients should be advised to avoid foods containing a very large amount of tyramine while taking recommended doses of AZILECT because of the potential for large increases in blood pressure including clinical syndromes referred to as hypertensive urgency, crisis, or emergency. AZILECT is a selective inhibitor of MAO-B at the recommended doses of 0.5 or 1 mg daily. Selectivity for inhibiting MAO-B diminishes in a dose-related manner as the dose is progressively increased above the recommended daily doses.

5.2 Serotonin Syndrome

Serotonin syndrome has been reported with concomitant use of an antidepressant (e.g., selective serotonin reuptake inhibitors-SSRIs, serotonin-norepinephrine reuptake inhibitors-SNRIs, tricyclic antidepressants, tetracyclic antidepressants, triazolopyridine antidepressants) and a nonselective MAOI (e.g., phenelzine, tranylcypromine) or selective MAO-B inhibitors, such as selegiline (Eldepryl) and rasagiline (AZILECT). Serotonin syndrome has also been reported with concomitant use of AZILECT with meperidine, tramadol, methadone, or propoxyphene. AZILECT is contraindicated for use with meperidine, tramadol, methadone, propoxyphene, and MAO inhibitors (MAOIs), including other selective MAO-B inhibitors [see Contraindications (4) and Drug Interactions (7.1, 7.2, 7.3)].

In the postmarketing period, potentially life-threatening serotonin syndrome has been reported in patients treated with antidepressants concomitantly with AZILECT. Concomitant use of AZILECT with one of many classes of antidepressants (e.g., SSRIs, SNRIs, triazolopyridine, tricyclic or tetracyclic antidepressants) is not recommended [see Drug Interactions (7.5)].

The symptoms of serotonin syndrome have included behavioral and cognitive/mental status changes (e.g., confusion, hypomania, hallucinations, agitation, delirium, headache, and coma), autonomic effects (e.g., syncope, shivering, sweating, high fever/hyperthermia, hypertension, tachycardia, nausea, diarrhea), and somatic effects (e.g., muscular rigidity, myoclonus, muscle twitching, hyperreflexia manifested by clonus, and tremor). Serotonin syndrome can result in death.

AZILECT clinical trials did not allow concomitant use of fluoxetine or fluvoxamine with AZILECT, and the potential drug interaction between AZILECT and antidepressants has not been studied systematically. Although a small number of AZILECT-treated patients were concomitantly exposed to antidepressants (tricyclics n=115; SSRIs n=141), the exposure, both in dose and number of subjects, was not adequate to rule out the possibility of an untoward reaction from combining these agents. At least 14 days should elapse between discontinuation of AZILECT and initiation of treatment with a SSRI, SNRI, tricyclic, tetracyclic, or triazolopyridine antidepressant. Because of the long half-lives of certain antidepressants (e.g., fluoxetine and its active metabolite), at least five weeks (perhaps longer, especially if fluoxetine has been prescribed chronically and/or at higher doses) should elapse between discontinuation of fluoxetine and initiation of AZILECT [see Drug Interactions (7.5)].

5.3 Falling Asleep During Activities of Daily Living and Somnolence

It has been reported that falling asleep while engaged in activities of daily living always occurs in a setting of preexisting somnolence, although patients may not give such a history. For this reason, prescribers should monitor patients for drowsiness or sleepiness, because some of the events occur well after initiation of treatment with dopaminergic medication. Prescribers should also be aware that patients may not acknowledge drowsiness or sleepiness until directly questioned about drowsiness or sleepiness during specific activities.

Cases of patients treated with AZILECT and other dopaminergic medications have reported falling asleep while engaged in activities of daily living including the operation of motor vehicles, which sometimes resulted in accidents. Although many of these patients reported somnolence while on AZILECT with other dopaminergic medications, some perceived that they had no warning signs, such as excessive drowsiness, and believed that they were alert immediately prior to the event. Some of these events have been reported more than 1-year after initiation of treatment.

In Study 3, somnolence was a common occurrence in patients receiving AZILECT and was more frequent in patients with Parkinson’s disease receiving AZILECT than in respective patients receiving placebo (6% AZILECT compared to 4% Placebo) [see Adverse Reactions (6.1)].

Before initiating treatment with AZILECT, patients should be advised of the potential to develop drowsiness and specifically asked about factors that may increase the risk with AZILECT such as concomitant sedating medications, the presence of sleep disorders, and concomitant medications that increase rasagiline plasma levels (e.g., ciprofloxacin) [see Drug Interactions (7.6)]. If a patient develops significant daytime sleepiness or episodes of falling asleep during activities that require active participation (e.g., driving a motor vehicle, conversations, eating), AZILECT should ordinarily be discontinued. If a decision is made to continue these patients on AZILECT, advise them to avoid driving and other potentially dangerous activities. There is insufficient information to establish that dose reduction will eliminate episodes of falling asleep while engaged in activities of daily living.

5.4 Ciprofloxacin or Other CYP1A2 Inhibitors

Rasagiline plasma concentrations may increase up to 2 fold in patients using concomitant ciprofloxacin and other CYP1A2 inhibitors. Patients taking concomitant ciprofloxacin or other CYP1A2 inhibitors should not exceed a dose of AZILECT 0.5 mg once daily [see Dosage and Administration (2.2), Drug Interactions (7.6), and Clinical Pharmacology (12.3)].

5.5 Hepatic Impairment

Rasagiline plasma concentration may increase in patients with hepatic impairment. Patients with mild hepatic impairment should be given the dose of AZILECT 0.5 mg once daily. AZILECT should not be used in patients with moderate or severe hepatic impairment [see Dosage and Administration (2.3) and Clinical Pharmacology (12.3)].

5.6 Hypotension / Orthostatic Hypotension

In Study 3, the incidence of orthostatic hypotension consisting of a systolic blood pressure decrease (≥ 30 mm Hg) or a diastolic blood pressure decrease (≥ 20 mm Hg) after standing was 13% with AZILECT (1 mg/day) compared to 9% with placebo [see Adverse Reactions (6.1)].

At the 1 mg dose, the frequency of orthostatic hypotension (at any time during the study) was approximately 44% for AZILECT vs 33% for placebo for mild to moderate systolic blood pressure decrements (≥ 20 mm Hg), 40% for AZILECT vs 33% for placebo for mild to moderate diastolic blood pressure decrements (≥ 10 mm Hg), 7% for AZILECT vs 3% for placebo for severe systolic blood pressure decrements (≥ 40 mm Hg), and 9% for AZILECT vs 6% for placebo for severe diastolic blood pressure decrements (≥ 20 mm Hg). There was also an increased risk for some of these abnormalities at the lower 0.5 mg daily dose and for an individual patient having mild to moderate or severe orthostatic hypotension for both systolic and diastolic blood pressure.

In Study 2 where AZILECT was given as an adjunct therapy in patients not taking concomitant levodopa, there were 5 reports of orthostatic hypotension in patients taking AZILECT 1 mg (3.1%) and 1 report in patients taking placebo (0.6%) [see Adverse Reactions (6.1)].

Clinical trial data further suggest that orthostatic hypotension occurs most frequently in the first two months of AZILECT treatment and tends to decrease over time.

Some patients treated with AZILECT experienced a mildly increased risk for significant decreases in blood pressure unrelated to standing but while supine.

The risk for post-treatment hypotension (e.g., systolic < 90 or diastolic < 50 mm Hg) combined with a significant decrease from baseline (e.g., systolic > 30 or diastolic > 20 mm Hg) was higher for AZILECT 1 mg (3.2%) compared to placebo (1.3%).

There was no clear increased risk for lowering of blood pressure or postural hypotension associated with AZILECT 1 mg/day as monotherapy.

When used as an adjunct to levodopa, postural hypotension was also reported as an adverse reaction in approximately 6% of patients treated with AZILECT 0.5 mg, 9% of patients treated with AZILECT 1 mg and 3% of patients treated with placebo. Postural hypotension led to drug discontinuation and premature withdrawal from clinical trials in one (0.7%) patient treated with AZILECT 1 mg/day, no patients treated with AZILECT 0.5 mg/day and no placebo-treated patients.

5.7 Dyskinesia

When used as an adjunct to levodopa, AZILECT may cause dyskinesia or potentiate dopaminergic side effects and exacerbate preexisting dyskinesia. In Study 3, the incidence of dyskinesia was 18% for patients treated with 0.5 mg or 1 mg AZILECT as an adjunct to levodopa and 10% for patients treated with placebo as an adjunct to levodopa. Decreasing the dose of levodopa may mitigate this side effect [see Adverse Reactions (6.1)].

5.8 Hallucinations / Psychotic-Like Behavior

In the monotherapy study (Study 1), the incidence of hallucinations reported as an adverse event was 1.3% in patients treated with AZILECT 1 mg and 0.7% in patients treated with placebo. In Study 1, the incidence of hallucinations reported as an adverse reaction and leading to drug discontinuation and premature withdrawal was 1.3% in patients treated with AZILECT 1 mg and 0% in placebo-treated patients.

When studied as an adjunct therapy without levodopa (Study 2), hallucinations were reported as an adverse reaction in 1.2% of patients treated with 1 mg/day AZILECT and 1.8% of patients treated with placebo. Hallucinations led to drug discontinuation and premature withdrawal from the clinical trial in 0.6% of patients treated with AZILECT 1 mg/day and in none of the placebo-treated patients.

When studied as an adjunct to levodopa (Study 3), the incidence of hallucinations was approximately 5% in patients treated with AZILECT 0.5 mg/day, 4% in patients treated with AZILECT 1 mg/day, and 3% in patients treated with placebo. The incidence of hallucinations leading to drug discontinuation and premature withdrawal was about 1% in patients treated with 0.5 mg AZILECT and 1 mg AZILECT/day, and 0% in placebo-treated patients [see Adverse Reactions (6.1)].

Postmarketing reports indicate that patients may experience new or worsening mental status and behavioral changes, which may be severe, including psychotic-like behavior during treatment with AZILECT or after starting or increasing the dose of AZILECT. Other drugs prescribed to improve the symptoms of Parkinson’s disease can have similar effects on thinking and behavior. This abnormal thinking and behavior can consist of one or more of a variety of manifestations including paranoid ideation, delusions, hallucinations, confusion, psychotic-like behavior, disorientation, aggressive behavior, agitation, and delirium.

Patients should be informed of the possibility of developing hallucinations and instructed to report them to their healthcare provider promptly should they develop.

Patients with a major psychotic disorder should ordinarily not be treated with AZILECT because of the risk of exacerbating the psychosis with an increase in central dopaminergic tone. In addition, many treatments for psychosis that decrease central dopaminergic tone may decrease the effectiveness of AZILECT [see Drug Interactions (7.8)].

Consider dose reduction or stopping the medication if a patient develops hallucinations or psychotic like behaviors while taking AZILECT.

5.9 Impulse Control / Compulsive Behaviors

Case reports suggest that patients can experience intense urges to gamble, increased sexual urges, intense urges to spend money, binge eating, and/or other intense urges, and the inability to control these urges while taking one or more of the medications, including AZILECT, that increase central dopaminergic tone and that are generally used for the treatment of Parkinson’s disease. In some cases, although not all, these urges were reported to have stopped when the dose was reduced or the medication was discontinued. Because patients may not recognize these behaviors as abnormal, it is important for prescribers to specifically ask patients or their caregivers about the development of new or increased gambling urges, sexual urges, uncontrolled spending, or other urges while being treated with AZILECT. Consider dose reduction or stopping the medication if a patient develops such urges while taking AZILECT.

5.10 Withdrawal-Emergent Hyperpyrexia and Confusion

A symptom complex resembling neuroleptic malignant syndrome (characterized by elevated temperature, muscular rigidity, altered consciousness, and autonomic instability), with no other obvious etiology, has been reported in association with rapid dose reduction, withdrawal of, or changes in drugs that increase central dopaminergic tone.

6 ADVERSE REACTIONS

The following adverse reactions are described in more detail in the Warnings and Precautions section of the label:

- Hypertension [see Warnings and Precautions (5.1)]
- Serotonin Syndrome [see Warnings and Precautions (5.2)]
- Falling Asleep During Activities of Daily Living and Somnolence [see Warnings and Precautions (5.3)]
- Hypotension / Orthostatic Hypotension [see Warnings and Precautions (5.6)]
- Dyskinesia [see Warnings and Precautions (5.7)]
- Hallucinations / Psychotic-Like Behavior [see Warnings and Precautions (5.8)]
- Impulse Control /Compulsive Behaviors [see Warnings and Precautions (5.9)]
- Withdrawal-Emergent Hyperpyrexia and Confusion [see Warnings and Precautions (5.10)]

6.1 Clinical Trials Experience

Because clinical trials are conducted under widely varying conditions, adverse reaction rates observed in the clinical trials of a drug cannot be directly compared to the incidence of adverse reactions in the clinical trials of another drug and may not reflect the rates of adverse reactions observed in practice.

During the clinical development of AZILECT, Parkinson’s disease patients received AZILECT as initial monotherapy (Study 1) and as adjunct therapy (Study 2, Study 3, Study 4). As the populations in these studies differ, not only in the adjunct use of dopamine agonists or levodopa during AZILECT treatment, but also in the severity and duration of their disease, the adverse reactions are presented separately for each study.

Monotherapy Use of AZILECT

In Study 1, approximately 5% of the 149 patients treated with AZILECT discontinued treatment due to adverse reactions compared to 2% of the 151 patients who received placebo.

The only adverse reaction that led to the discontinuation of more than one patient was hallucinations.

The most commonly observed adverse reactions in Study 1 (incidence in AZILECT-treated patients 3% or greater than the incidence in placebo-treated patients) included flu syndrome, arthralgia, depression, and dyspepsia. Table 1 lists adverse reactions that occurred in 2% or greater of patients receiving AZILECT as monotherapy and were numerically more frequent than in the placebo group in Study 1.

Table 1: Adverse Reactions* in Study 1
 | AZILECT 1 mg (N=149) | Placebo (N=151)
 | % of Patients | % of Patients
Headache | 14 | 12
Arthralgia | 7 | 4
Dyspepsia | 7 | 4
Depression | 5 | 2
Fall | 5 | 3
Flu syndrome | 5 | 1
Conjunctivitis | 3 | 1
Fever | 3 | 1
Gastroenteritis | 3 | 1
Rhinitis | 3 | 1
Arthritis | 2 | 1
Ecchymosis | 2 | 0
Malaise | 2 | 0
Neck Pain | 2 | 0
Paresthesia | 2 | 1
Vertigo | 2 | 1

*Incidence 2% or greater in AZILECT 1 mg group and numerically more frequent than in placebo group

There were no significant differences in the safety profile based on age or gender.

Adjunct Use of AZILECT

AZILECT was studied as an adjunct therapy without levodopa (Study 2), or as an adjunct therapy to levodopa, with some patients also taking dopamine agonists, COMT inhibitors, anticholinergics, or amantadine (Study 3 and Study 4).

In Study 2, approximately 8% of the 162 patients treated with AZILECT discontinued treatment due to adverse reactions compared to 4% of the 164 patients who received placebo.

Adverse reactions that led to the discontinuation of more than one patient were nausea and dizziness.

The most commonly observed adverse reactions in Study 2 (incidence in AZILECT-treated patients 3% or greater than incidence in placebo-treated patients) included peripheral edema, fall, arthralgia, cough, and insomnia. Table 2 lists adverse reactions that occurred in 2% or greater in patients receiving AZILECT as adjunct therapy without levodopa and numerically more frequent than in the placebo group in Study 2.

Table 2: Adverse Reactions* in Study 2
 | AZILECT 1 mg (N=162) | Placebo; (N=164)
 | % of Patients | % of Patients
Dizziness | 7 | 6
Peripheral edema | 7 | 4
Headache | 6 | 4
Nausea | 6 | 4
Fall | 6 | 1
Arthralgia | 5 | 2
Back pain | 4 | 3
Cough | 4 | 1
Insomnia | 4 | 1
Upper respiratory tract infection | 4 | 2
Orthostatic hypotension | 3 | 1

*Incidence 2% or greater in AZILECT 1 mg group and numerically more frequent than in placebo group

There were no significant differences in the safety profile based on age or gender.

In Study 3, adverse event reporting was considered more reliable than Study 4; therefore, only the adverse event data from Study 3 are presented below.

In Study 3, approximately 9% of the 164 patients treated with AZILECT 0.5 mg/day and 7% of the 149 patients treated with AZILECT 1 mg/day discontinued treatment due to adverse reactions, compared to 6% of the 159 patients who received placebo. The adverse reactions that led to discontinuation of more than one AZILECT-treated patient were diarrhea, weight loss, hallucination, and rash.

The most commonly observed adverse reactions in Study 3 (incidence in AZILECT-treated patients 3% or greater than the incidence in placebo-treated patients) included dyskinesia, accidental injury, weight loss, postural hypotension, vomiting, anorexia, arthralgia, abdominal pain, nausea, constipation, dry mouth, rash, abnormal dreams, fall, and tenosynovitis.

Table 3 lists adverse reactions that occurred in 2% or greater of patients treated with AZILECT 1 mg/day and that were numerically more frequent than the placebo group in Study 3.

Table 3: Adverse Reactions* in Study 3
 | AZILECT 1 mg; (N=149) | AZILECT 0.5 mg (N=164) | Placebo (N=159)
 | % of Patients | % of Patients | % of Patients
Dyskinesia | 18 | 18 | 10
Accidental injury | 12 | 8 | 5
Nausea | 12 | 10 | 8
Headache | 11 | 8 | 10
Fall | 11 | 12 | 8
Weight loss | 9 | 2 | 3
Constipation | 9 | 4 | 5
Postural hypotension | 9 | 6 | 3
Arthralgia | 8 | 6 | 4
Vomiting | 7 | 4 | 1
Dry mouth | 6 | 2 | 3
Rash | 6 | 3 | 3
Somnolence | 6 | 4 | 4
Abdominal pain | 5 | 2 | 1
Anorexia | 5 | 2 | 1
Diarrhea | 5 | 7 | 4
Ecchymosis | 5 | 2 | 3
Dyspepsia | 5 | 4 | 4
Paresthesia | 5 | 2 | 3
Abnormal dreams | 4 | 1 | 1
Hallucinations | 4 | 5 | 3
Ataxia | 3 | 6 | 1
Dyspnea | 3 | 5 | 2
Infection | 3 | 2 | 2
Neck pain | 3 | 1 | 1
Sweating | 3 | 2 | 1
Tenosynovitis | 3 | 1 | 0
Dystonia | 3 | 2 | 1
Gingivitis | 2 | 1 | 1
Hemorrhage | 2 | 1 | 1
Hernia | 2 | 1 | 1
Myasthenia | 2 | 2 | 1

*Incidence 2% or greater in AZILECT 1 mg group and numerically more frequent than in placebo group

Several of the more common adverse reactions seemed dose-related, including weight loss, postural hypotension, and dry mouth.

There were no significant differences in the safety profile based on age or gender.

During all Parkinson’s disease phase 2/3 clinical trials, the long-term safety profile was similar to that observed with shorter duration exposure.

6.2 Postmarketing Experience

The following adverse reactions have been identified during postapproval use of AZILECT. Because these reactions are reported voluntarily from a population of uncertain size, it is not always possible to reliably estimate their frequency or establish a causal relationship to drug exposure.

Skin and Subcutaneous Tissue Disorders: Melanoma

7 DRUG INTERACTIONS

7.1 Meperidine

Serious, sometimes fatal reactions have been precipitated with concomitant use of meperidine (e.g., Demerol and other tradenames) and MAO inhibitors including selective MAO-B inhibitors [see Contraindications (4)].

7.2 Dextromethorphan

The concomitant use of AZILECT and dextromethorphan was not allowed in clinical studies. The combination of MAO inhibitors and dextromethorphan has been reported to cause brief episodes of psychosis or bizarre behavior. Therefore, in view of AZILECT’s MAO inhibitory activity, dextromethorphan is contraindicated for use with AZILECT [see Contraindications (4)].

7.3 MAO Inhibitors

AZILECT is contraindicated for use with other MAO inhibitors because of the increased risk of nonselective MAO inhibition that may lead to a hypertensive crisis [see Contraindications (4)].

7.4 Sympathomimetic Medications

The concomitant use of AZILECT and sympathomimetic medications was not allowed in clinical studies. Severe hypertensive reactions have followed the administration of sympathomimetics and nonselective MAO inhibitors. Hypertensive crisis has been reported in patients taking the recommended dose of AZILECT and sympathomimetic medications. Severe hypertension has been reported in patients taking the recommended dose of AZILECT and ophthalmic drops containing sympathomimetic medications.

Because AZILECT is a selective MAOI, hypertensive reactions are not ordinarily expected with the concomitant use of sympathomimetic medications. Nevertheless, caution should be exercised when concomitantly using recommended doses of AZILECT with any sympathomimetic medications including nasal, oral, and ophthalmic decongestants and cold remedies.

7.5 Antidepressants

Concomitant use of AZILECT with one of many classes of antidepressants (e.g., SSRIs, SNRIs, triazolopyridine, tricyclic, or tetracyclic antidepressants) is not recommended [see Warnings and Precautions (5.2) and Clinical Pharmacology (12.3)]. Concomitant use of AZILECT and MAO inhibitors is contraindicated [see Contraindications (4)].

7.6 Ciprofloxacin or Other CYP1A2 Inhibitors

Rasagiline plasma concentrations may increase up to 2 fold in patients using concomitant ciprofloxacin and other CYP1A2 inhibitors. This could result in increased adverse events. Patients taking concomitant ciprofloxacin or other CYP1A2 inhibitors should not exceed a dose of AZILECT 0.5 mg once daily [see Warnings and Precautions (5.4) and Clinical Pharmacology (12.3)].

7.7 Tyramine/Rasagiline Interaction

MAO in the gastrointestinal tract and liver (primarily type A) provides protection from exogenous amines (e.g., tyramine) that have the capacity, if absorbed intact, to cause a tyramine reaction with hypertension including clinical syndromes referred to as hypertensive urgency, crisis, or emergency. Foods and medications containing large amounts of exogenous amines (e.g., from fermented cheese, herring, over-the-counter cough/cold medications) may cause release of norepinephrine resulting in a rise in systemic blood pressure.

Results of a special tyramine challenge study indicate that rasagiline is selective for MAO-B at recommended doses and can be used without dietary tyramine restriction. However, certain foods may contain very high amounts (i.e., 150 mg or greater) of tyramine and could potentially cause a hypertensive reaction in individual patients taking AZILECT due to increased sensitivity to tyramine. Selectivity for inhibiting MAO-B diminishes in a dose-related manner as the dose is progressively increased above the recommended daily doses.

There were no cases of hypertensive crisis in the clinical development program associated with 1 mg daily AZILECT treatment, in which most patients did not follow dietary tyramine restriction.

There have been postmarketing reports of patients who experienced significantly elevated blood pressure (including rare cases of hypertensive crisis) after ingestion of unknown amounts of tyramine-rich foods while taking recommended doses of AZILECT. Patients should be advised to avoid foods containing a very large amount of tyramine while taking recommended doses of AZILECT [see Warnings and Precautions (5.1)].

7.8 Dopaminergic Antagonists

It is possible that dopamine antagonists, such as antipsychotics or metoclopramide, could diminish the effectiveness of AZILECT.

8 USE IN SPECIFIC POPULATIONS

8.1 Pregnancy

Risk Summary

There are no adequate data on the developmental risks associated with the use of AZILECT in pregnant women. In animal studies, oral administration of rasagiline to rats during gestation and lactation resulted in decreased survival and reduced body weight in the offspring at doses similar to those used clinically. When administered to pregnant animals in combination with levodopa/carbidopa, there were increased incidences of fetal skeletal variations in rats and increases in embryofetal death and cardiovascular abnormalities in rabbits [see Data].

In the US general population, the estimated background risk of major birth defects and miscarriage in clinically recognized pregnancies is 2% to 4% and 15% to 20%, respectively. The background risks of major birth defects and miscarriage for the indicated population is unknown.

Data

Animal Data

In a combined mating/fertility and embryofetal development study in pregnant rats, no effect on embryofetal development was observed at oral doses up to 3 mg/kg/day (approximately 30 times the plasma exposure (AUC) in humans at the maximum recommended human dose [MRHD, 1 mg/day]).

In pregnant rabbits administered rasagiline throughout the period of organogenesis at oral doses of up to 36 mg/kg/day, no developmental toxicity was observed. At the highest dose tested, the plasma AUC was approximately 800 times that in humans at the MRHD.

In pregnant rats administered rasagiline (0, 0.1, 0.3, 1 mg/kg/day) orally during gestation and lactation, offspring survival was decreased and offspring body weight was reduced at 0.3 mg/kg/day and 1 mg/kg/day (10 and 16 times the plasma AUC in humans at the MRHD). The no-effect dose (0.1 mg/kg) for adverse developmental effects is similar to the MRHD on a body surface area (mg/m^2) basis. The effect of rasagiline on physical and behavioral development was not adequately assessed in this study.

Rasagiline may be given as an adjunct therapy to levodopa/carbidopa treatment. In pregnant rats administered rasagiline (0, 0.1, 0.3, 1 mg/kg/day) and levodopa/carbidopa (80/20 mg/kg/day) (alone and in combination) orally throughout the period of organogenesis, there was an increased incidence of fetal skeletal variations in fetuses from rats treated with rasagiline in combination with levodopa/carbidopa at 1/80/20 mg/kg/day (approximately 8 times the rasagiline plasma AUC in humans at the MRHD and similar to the MRHD of levodopa/carbidopa [800/200 mg/day] on a mg/m^2 basis). In pregnant rabbits dosed orally throughout the period of organogenesis with rasagiline alone (3 mg/kg) or in combination with levodopa/carbidopa (rasagiline: 0.1, 0.6, 1.2 mg/kg, levodopa/carbidopa: 80/20 mg/kg/day), an increase in embryofetal death was noted at rasagiline doses of 0.6 and 1.2 mg/kg/day when administered in combination with levodopa/carbidopa (approximately 7 and 13 times, respectively, the rasagiline plasma AUC in humans at the MRHD). There was an increase in cardiovascular abnormalities with levodopa/carbidopa alone (similar to the MRHD on a mg/m^2 basis) and to a greater extent when rasagiline (at all doses; 1-13 times the rasagiline plasma AUC in humans at the MRHD) was administered in combination with levodopa/carbidopa.

8.2 Lactation

Risk Summary

There are no data on the presence of rasagiline in human milk or the effects on the breastfed infant. In rats, rasagiline was shown to inhibit prolactin secretion. The clinical relevance in humans is unknown, and there are no data on the effects of rasagiline on prolactin secretion or milk production in humans.

The developmental and health benefits of breastfeeding should be considered along with the mother’s clinical need for AZILECT and any potential adverse effects on the breastfed infant from AZILECT or from the underlying maternal condition.

8.4 Pediatric Use

The safety and effectiveness in pediatric patients have not been established.

8.5 Geriatric Use

Approximately half of patients in clinical trials were 65 years and over. There were no significant differences in the safety profile of the geriatric and nongeriatric patients.

8.6 Hepatic Impairment

Rasagiline plasma concentration may be increased in patients with mild (up to 2 fold, Child-Pugh score 5-6), moderate (up to 7 fold, Child-Pugh score 7-9), and severe (Child-Pugh score 10-15) hepatic impairment. Patients with mild hepatic impairment should not exceed a dose of 0.5 mg/day. AZILECT should not be used in patients with moderate or severe hepatic impairment [see Dosage and Administration (2.3), Warnings and Precautions (5.5) and Clinical Pharmacology (12.3)].

8.7 Renal Impairment

Dose adjustment of AZILECT is not required for patients with mild or moderate renal impairment because AZILECT plasma concentrations are not increased in patients with moderate renal impairment. Rasagiline has not been studied in patients with severe renal impairment [see Clinical Pharmacology (12.3)].

9 DRUG ABUSE AND DEPENDENCE

9.1 Controlled Substance

AZILECT is not a controlled substance.

9.2 Abuse

Studies conducted in mice and rats did not reveal any potential for drug abuse and dependence. Clinical trials have not revealed any evidence of the potential for abuse, tolerance, or physical dependence; however, systematic studies in humans designed to evaluate these effects have not been performed.

9.3 Dependence

Studies conducted in mice and rats did not reveal any potential for drug abuse and dependence. Clinical trials have not revealed any evidence of the potential for abuse, tolerance, or physical dependence; however, systematic studies in humans designed to evaluate these effects have not been performed.

10 OVERDOSAGE

In a dose escalation study in patients on chronic levodopa therapy treated with 10 mg of AZILECT there were three reports of cardiovascular side effects (including hypertension and postural hypotension) which resolved following treatment discontinuation.

Although no cases of overdose have been observed with AZILECT during the clinical development program, the following description of presenting symptoms and clinical course is based upon overdose descriptions of nonselective MAO inhibitors.

The signs and symptoms of nonselective MAOI overdose may not appear immediately. Delays of up to 12 hours after ingestion of drug and the appearance of signs may occur. The peak intensity of the syndrome may not be reached until for a day following the overdose. Death has been reported following overdose; therefore, immediate hospitalization, with continuous patient observation and monitoring for at least two days following the ingestion of such drugs in overdose, is strongly recommended.

The severity of the clinical signs and symptoms of MAOI overdose varies and may be related to the amount of drug consumed. The central nervous and cardiovascular systems are prominently involved.

Signs and symptoms of MAOI overdose may include: drowsiness, dizziness, faintness, irritability, hyperactivity, agitation, severe headache, hallucinations, trismus, opisthotonos, convulsions, and coma; rapid and irregular pulse, hypertension, hypotension and vascular collapse; precordial pain, respiratory depression and failure, hyperpyrexia, diaphoresis, and cool, clammy skin.

There is no specific antidote for AZILECT overdose. The following suggestions are offered based upon the assumption that AZILECT overdose may be modeled after nonselective MAO inhibitor poisoning. Treatment of overdose with nonselective MAO inhibitors is symptomatic and supportive. Respiration should be supported by appropriate measures, including management of the airway, use of supplemental oxygen, and mechanical ventilatory assistance, as required. Body temperature should be monitored closely. Intensive management of hyperpyrexia may be required. Maintenance of fluid and electrolyte balance is essential. For this reason, in cases of overdose with AZILECT, dietary tyramine restriction should be observed for several weeks to reduce the risk of hypertensive tyramine reaction.

A poison control center should be called for the most current treatment guidelines.

A postmarketing report described a single patient who developed a nonfatal serotonin syndrome after ingesting 100 mg of AZILECT in a suicide attempt. Another patient who was treated in error with 4 mg AZILECT daily and tramadol also developed a serotonin syndrome. One patient who was treated in error with 3 mg AZILECT daily experienced alternating episodes of vascular fluctuations consisting of hypertension and orthostatic hypotension.

11 DESCRIPTION

AZILECT® tablets contain rasagiline (as the mesylate), a propargylamine-based drug indicated for the treatment of idiopathic Parkinson’s disease. Rasagiline mesylate is designated chemically as: 1H-Inden-1-amine, 2, 3-dihydro-N-2-propynyl-, (1R)-, methanesulfonate. The empirical formula of rasagiline mesylate is C12H13N•CH4SO3 and its molecular weight is 267.34.

Its structural formula is:

Rasagiline mesylate is a white to off-white powder, freely soluble in water or ethanol and sparingly soluble in isopropanol. Each AZILECT tablet for oral administration contains 0.5 mg or 1 mg of rasagiline (equivalent to 0.78 mg or 1.56 mg of rasagiline mesylate).

Each AZILECT tablet also contains the following inactive ingredients: mannitol, starch, pregelatinized starch, colloidal silicon dioxide, stearic acid, and talc.

12 CLINICAL PHARMACOLOGY

12.1 Mechanism of Action

AZILECT is a selective, irreversible MAO-B inhibitor indicated for the treatment of idiopathic Parkinson’s disease. The results of a clinical trial designed to examine the effects of AZILECT on blood pressure when it is administered with increasing doses of tyramine indicates the functional selectivity can be incomplete when healthy subjects ingest large amounts of tyramine while receiving recommended doses of AZILECT. The selectivity for inhibiting MAO-B diminishes in a dose-related manner.

MAO, a flavin-containing enzyme, is classified into two major molecular species, A and B, and is localized in mitochondrial membranes throughout the body in nerve terminals, brain, liver and intestinal mucosa. MAO regulates the metabolic degradation of catecholamines and serotonin in the CNS and peripheral tissues. MAO-B is the major form in the human brain. In ex vivo animal studies in brain, liver, and intestinal tissues, rasagiline was shown to be a potent, irreversible monoamine oxidase type B (MAO-B) selective inhibitor. Rasagiline at the recommended therapeutic dose was also shown to be a potent and irreversible inhibitor of MAO-B in platelets. The precise mechanisms of action of rasagiline are unknown. One mechanism is believed to be related to its MAO-B inhibitory activity, which causes an increase in extracellular levels of dopamine in the striatum. The elevated dopamine level and subsequent increased dopaminergic activity are likely to mediate rasagiline’s beneficial effects seen in models of dopaminergic motor dysfunction.

12.2 Pharmacodynamics

Tyramine Challenge Test

Results of a tyramine challenge study indicate that rasagiline at recommended doses is relatively selective for inhibiting MAO-B and can be used without dietary tyramine restriction. However, certain foods (e.g., aged cheeses, such as Stilton cheese) may contain very high amounts of tyramine (i.e., 150 mg or greater) and could potentially cause severe hypertension caused by tyramine interaction in patients taking AZILECT due to mild increased sensitivity to tyramine at recommended doses. Relative selectivity of AZILECT for inhibiting MAO-B diminished in a dose-related manner as the dose progressively increased above the highest recommended daily dose (1 mg) [see Warnings and Precautions (5.1) and Drug Interactions (7.7)].

Platelet MAO Activity in Clinical Studies

Studies in healthy subjects and in Parkinson’s disease patients have shown that rasagiline inhibits platelet MAO-B irreversibly. The inhibition lasts at least 1 week after last dose. Almost 25-35% MAO-B inhibition was achieved after a single rasagiline dose of 1 mg/day and more than 55% of MAO-B inhibition was achieved after a single rasagiline dose of 2 mg/day. Over 90% inhibition was achieved 3 days after rasagiline daily dosing at 2 mg/day and this inhibition level was maintained 3 days postdose. Multiple doses of rasagiline of 0.5, 1, and 2 mg per day resulted in complete MAO-B inhibition.

12.3 Pharmacokinetics

Rasagiline in the range of 1-6 mg demonstrated a more than proportional increase in AUC, while Cmax was dose proportional. Rasagiline mean steady-state half life is 3 hours but there is no correlation of pharmacokinetics with its pharmacological effect because of its irreversible inhibition of MAO-B.

Absorption

Rasagiline is rapidly absorbed, reaching peak plasma concentration (Cmax) in approximately 1 hour. The absolute bioavailability of rasagiline is about 36%.

Food does not affect the Tmax of rasagiline, although Cmax and exposure (AUC) are decreased by approximately 60% and 20%, respectively, when the drug is taken with a high fat meal. Because AUC is not significantly affected, AZILECT can be administered with or without food.

Distribution

The mean volume of distribution at steady-state is 87 L, indicating that the tissue binding of rasagiline is in excess of plasma protein binding. Plasma protein binding ranges from 88-94% with mean extent of binding of 61-63% to human albumin over the concentration range of 1-100 ng/mL.

Metabolism and Elimination

Rasagiline undergoes almost complete biotransformation in the liver prior to excretion. The metabolism of rasagiline proceeds through two main pathways: N-dealkylation and/or hydroxylation to yield 1-aminoindan (AI), 3-hydroxy-N-propargyl-1 aminoindan (3-OH-PAI) and 3-hydroxy-1-aminoindan (3-OH-AI). In vitro experiments indicate that both routes of rasagiline metabolism are dependent on the cytochrome P450 (CYP) system, with CYP1A2 being the major isoenzyme involved in rasagiline metabolism. Glucuronide conjugation of rasagiline and its metabolites, with subsequent urinary excretion, is the major elimination pathway.

After oral administration of ^14C-labeled rasagiline, elimination occurred primarily via urine and secondarily via feces (62% of total dose in urine and 7% of total dose in feces over 7 days), with a total calculated recovery of 84% of the dose
over a period of 38 days. Less than 1% of rasagiline was excreted as unchanged drug in urine.

Specific Populations

Hepatic Impairment

Following repeat dose administration (7 days) of rasagiline (1 mg/day) in subjects with mild hepatic impairment (Child-Pugh score 5-6), AUC and Cmax were increased by 2 fold and 1.4 fold, respectively, compared to healthy subjects. In subjects with moderate hepatic impairment (Child-Pugh score 7-9), AUC and Cmax were increased by 7 fold and 2 fold, respectively, compared to healthy subjects [see Dosage and Administration (2.3) and Warnings and Precautions (5.5)].

Renal Impairment

Following repeat dose administration (8 days) of rasagiline (1 mg/day) in subjects with moderate renal impairment, rasagiline exposure (AUC) was similar to rasagiline exposure in healthy subjects, while the major metabolite 1-AI exposure (AUC) was increased 1.5- fold in subjects with moderate renal impairment, compared to healthy subjects. Because 1-AI is not an MAO inhibitor, no dose adjustment is needed for patients with mild and moderate renal impairment. Data are not available for patients with severe renal impairment.

Elderly

Since age has little influence on rasagiline pharmacokinetics, it can be administered at the recommended dose in the elderly (≥ 65 years).

Pediatric

AZILECT has not been investigated in patients below 18 years of age.

Gender

The pharmacokinetic profile of rasagiline is similar in men and women.

Drug-Drug Interactions

Levodopa

A study in Parkinson’s disease patients, in which the effect of levodopa/carbidopa (LD/CD) on rasagiline pharmacokinetics at steady state was investigated, showed that the pharmacokinetics of rasagiline were not affected by concomitant administration of LD/CD.

Effect of Other Drugs on the Metabolism of AZILECT

In vitro metabolism studies showed that CYP1A2 was the major enzyme responsible for the metabolism of rasagiline. There is the potential for inhibitors of this enzyme to alter AZILECT clearance when coadministered [see Dosage and Administration (2.2) and Warnings and Precautions (5.4)].

Ciprofloxacin: When ciprofloxacin, an inhibitor of CYP1A2, was administered to healthy volunteers (n=12) at 500 mg (BID) with rasagiline at 2 mg/day, the AUC of rasagiline increased by 83% and there was no change in the elimination half life [see Dosage and Administration (2.2) and Warnings and Precautions (5.4)].

Theophylline: Coadministration of rasagiline 1 mg/day and theophylline, a substrate of CYP1A2, up to 500 mg twice daily to healthy subjects (n=24) did not affect the pharmacokinetics of either drug.

Antidepressants: Severe CNS toxicity (occasionally fatal) associated with hyperpyrexia as part of a serotonin syndrome, has been reported with combined treatment of an antidepressant (e.g., from one of many classes including tricyclic or tetracyclic antidepressants, SSRIs, SNRIs, triazolopyridine antidepressants) and nonselective MAOI or a selective MAO-B inhibitor [see Warnings and Precautions (5.2)].

Effect of AZILECT on Other Drugs

No additional in vivo trials have investigated the effect of AZILECT on other drugs metabolized by the cytochrome P450 enzyme system. In vitro studies showed that rasagiline at a concentration of 1 mcg/mL (equivalent to a level that is 160 times the average Cmax ~ 5.9-8.5 ng/mL in Parkinson’s disease patients after 1 mg rasagiline multiple dosing) did not inhibit cytochrome P450 isoenzymes, CYP1A2, CYP2A6, CYP2C9, CYP2C19, CYP2D6, CYP2E1, CYP3A4 and CYP4A. These results indicate that rasagiline is unlikely to cause any clinically significant interference with substrates of these enzymes.

13 NONCLINICAL TOXICOLOGY

13.1 Carcinogenesis, Mutagenesis, Impairment of Fertility

Carcinogenesis

Two-year carcinogenicity studies were conducted in mice at oral doses of 0, 1, 15, and 45 mg/kg/day and in rats at oral doses of 0.3, 1, and 3 mg/kg/day (males) or 0, 0.5, 2, 5, and 17 mg/kg/day (females). In rats, there was no increase in tumors at any dose tested. Plasma exposures (AUC) at the highest dose tested were approximately 33 and 260 times, in male and female rats, respectively, that in humans at the maximum recommended human dose (MRHD) of 1 mg/day.

In mice, there was an increase in lung tumors (combined adenomas/carcinomas) at 15 and 45 mg/kg in males and females. At the lowest dose tested, plasma AUCs were approximately 5 times those expected in humans at the MRHD.

The carcinogenic potential of rasagiline administered in combination with levodopa/carbidopa has not been examined.

Mutagenesis

Rasagiline was reproducibly clastogenic in in vitro chromosomal aberration assays in human lymphocytes in the presence of metabolic activation and was mutagenic and clastogenic in the in vitro mouse lymphoma tk assay in the absence and presence of metabolic activation. Rasagiline was negative in the in vitro bacterial reverse mutation (Ames) assay and in the in vivo micronucleus assay in mice. Rasagiline was also negative in the in vivo micronucleus assay in mice when administered in combination with levodopa/carbidopa.

Impairment of Fertility

Rasagiline had no effect on mating performance or fertility in rats treated prior to and throughout the mating period and continuing in females through gestation day 17 at oral doses of up to 3 mg/kg/day (approximately 30 times the plasma AUC in humans at the MRHD). The effect of rasagiline administered in combination with levodopa/carbidopa on mating and fertility has not been examined.

14 CLINICAL STUDIES

The effectiveness of AZILECT for the treatment of Parkinson’s disease was established in four 18- to 26-week, randomized, placebo-controlled trials, as initial monotherapy or adjunct therapy.

14.1 Monotherapy Use of AZILECT

Study 1 was a double-blind, randomized, fixed-dose parallel group, 26-week study in early Parkinson’s disease patients not receiving any concomitant dopaminergic therapy at the start of the study. The majority of the patients were not treated with medications for Parkinson’s disease before receiving AZILECT.

In Study 1, 404 patients were randomly assigned to receive placebo (138 patients), AZILECT 1 mg/day (134 patients) or AZILECT 2 mg/day (132 patients). Patients were not allowed to take levodopa, dopamine agonists, selegiline, or amantadine, but could take stable doses of anticholinergic medication, if necessary. The average Parkinson’s disease duration was approximately 1 year (range 0 to 11 years).

The primary measure of effectiveness was the change from baseline in the total score of the Unified Parkinson’s Disease Rating Scale (UPDRS), [mentation (Part I) + activities of daily living (ADL) (Part II) + motor function (Part III)]. The UPDRS is a multi-item rating scale that measures the ability of a patient to perform mental and motor tasks as well as activities of daily living. A reduction in the score represents improvement and a beneficial change from baseline appears as a negative number.

AZILECT (1 or 2 mg once daily) was superior to placebo on the primary measure of effectiveness in patients receiving six months of treatment and not on dopaminergic therapy. The effectiveness of AZILECT 1 mg and 2 mg was comparable. Table 4 shows the results of Study 1. There were no differences in effectiveness based on age or gender between AZILECT 1 mg/day and placebo.

Table 4: Change in Total UPDRS Score in Study 1
 | Baseline score | Change from baseline to termination score | p-value vs. placebo
Placebo | 24.5 | 3.9 | ---
AZILECT 1 mg | 24.7 | 0.1 | 0.0001
AZILECT 2 mg | 25.9 | 0.7 | 0.0001

14.2 Adjunct Use of AZILECT

Study 2 was a double-blind, randomized, placebo-controlled, parallel group, 18-week study, investigating AZILECT 1 mg as adjunct therapy to dopamine agonists without levodopa. Patients were on a stable dose of dopamine agonist (ropinirole, mean 8 mg/day or pramipexole, mean 1.5 mg/day) therapy for ≥ 30 days, but at doses not sufficient to control Parkinson’s disease symptoms.

In Study 2, 321 patients randomly received placebo (162 patients) or AZILECT 1 mg/day (159 patients) and had a post-baseline assessment. The average Parkinson’s disease duration was approximately 2 years (range 0.1 to 14.5 years).

The primary measure of effectiveness was the change from baseline in the total score of the Unified Parkinson’s Disease Rating Scale (UPDRS) [mentation (Part I) + activities of daily living (ADL) (Part II) + motor function (Part III)].

In Study 2, AZILECT 1 mg was superior to placebo on the primary measure of effectiveness (see Table 5).

Table 5: Change in Total UPDRS Score in Study 2
 | Baseline score | Change from baseline to termination score* | p-value vs. placebo
Placebo | 29.8 | –1.2 | ---
AZILECT1 mg | 32.1 | –3.6 | 0.012

*A negative change from baseline indicates improvement in the UPDRS

Secondary outcome assessment of the individual subscales of the UPDRS indicates that the UPDRS Part III motor subscale was primarily responsible for the overall AZILECT effect on the UPDRS score (see Table 6).

Table 6: Secondary Measures of Effectiveness in Study 2
 | Baseline (score) | Change from baseline to termination score
UPDRS Part II ADL (Activities of Daily Living) subscale score
Placebo | 7.9 | 0.4
AZILECT 1 mg | 8.6 | -0.3
UPDRS Part III Motor subscale score
Placebo | 20.4 | -1.2
AZILECT 1 mg | 22.2 | -3.7

Study 3 and Study 4 were randomized, multinational trials conducted in more advanced Parkinson’s disease patients treated chronically with levodopa and experiencing motor fluctuations (including but not limited to, end of dose “wearing off,” sudden or random “off,” etc.). Study 3 was conducted in North America (U.S. and Canada) and compared AZILECT 0.5 mg and 1 mg daily to placebo. Study 4 was conducted outside of North America in Europe, Argentina, and Israel, and compared AZILECT 1 mg daily to placebo.

Patients had Parkinson’s disease for an average of 9 years (range 5 months to 33 years), had taken levodopa for an average of 8 years (range 5 months to 32 years), and had motor fluctuations for approximately 3 to 4 years (range 1 month to 23 years). Patients kept home Parkinson’s disease diaries just prior to baseline and at specified intervals during the trial. Diaries recorded one of the following four conditions for each half-hour interval over a 24-hour period: “ON” (period of relatively good function and mobility) as either “ON” with no dyskinesia or without troublesome dyskinesia, or “ON” with troublesome dyskinesia, “OFF” (period of relatively poor function and mobility) or asleep. “Troublesome” dyskinesia is defined as dyskinesia that interferes with the patient’s daily activity. All patients had inadequate control of their motor symptoms with motor fluctuations typical of advanced stage disease despite receiving levodopa/decarboxylase inhibitor. The average dose of levodopa taken with a decarboxylase inhibitor was approximately 700 to 800 mg (range 150 to 3000 mg/day). Patients continued their stable doses of additional anti-PD medications at entry into the trials. Approximately 65% of patients in both studies were also taking a dopamine agonist. In the North American study (Study 3), approximately 35% of patients took entacapone with levodopa/decarboxylase inhibitor. The majority of patients taking entacapone were also taking a dopamine agonist.

In Study 3 and Study 4, the primary measure of effectiveness was the change in the mean number of hours spent in the “OFF” state at baseline compared to the mean number of hours spent in the “OFF” state during the treatment period.

In Study 3, patients were randomly assigned to receive placebo (159 patients), AZILECT 0.5 mg/day (164 patients), or AZILECT 1 mg/day (149 patients) for 26 weeks. Patients averaged 6 hours daily in the “OFF” state at baseline as confirmed by home diaries.

In Study 4, patients were randomly assigned to receive placebo (229 patients), AZILECT 1 mg/day (231 patients) or a COMT inhibitor (active comparator), taken along with scheduled doses of levodopa/decarboxylase inhibitor (227 patients) for 18 weeks. Patients averaged 5.6 hours daily in the “OFF” state at baseline as confirmed by home diaries.

In Study 3 and Study 4, AZILECT 1 mg once daily reduced “OFF” time compared to placebo when added to levodopa in patients experiencing motor fluctuations (Tables 7 and 8). The lower dose (0.5 mg) of AZILECT also significantly reduced “OFF” time (Table 7), but had a numerically smaller effect than the 1 mg dose of AZILECT. In Study 4, the active comparator also reduced “OFF” time when compared to placebo.

Table 7: Change in mean total daily “OFF” time in Study 3
 | Baseline (hours) | Change from baseline to treatment period (hours) | p-value vs. placebo
Placebo | 6.0 | -0.9 | ---
AZILECT 0.5 mg | 6.0 | -1.4 | 0.0199
AZILECT 1.0 mg | 6.3 | -1.9 | < 0.0001

Table 8: Change in mean total daily “OFF” time in Study 4
 | Baseline (hours) | Change from baseline to treatment period (hours) | p-value vs. placebo
Placebo | 5.5 | - 0.40 | ---
AZILECT 1.0 mg | 5.6 | -1.2 | 0.0001

In Study 3 and Study 4, dose reduction of levodopa was allowed within the first 6 weeks, if dopaminergic side effects developed including dyskinesia or hallucinations. In Study 3, the levodopa dose was reduced in 8% of patients in the placebo group and in 16% and 17% of patients in the 0.5 mg/day and 1 mg/day AZILECT groups, respectively. When levodopa was reduced, the dose was reduced by 7%, 9%, and 13% in the placebo, 0.5 mg/day, and 1 mg/day groups, respectively. In Study 4, levodopa dose reduction occurred in 6% of patients in the placebo group and in 9% in the AZILECT 1 mg/day groups, respectively. When levodopa was reduced, it was reduced by 13% and 11% in the placebo and the AZILECT groups, respectively.

There were no differences in effectiveness based on age or gender between AZILECT 1 mg/day and placebo.

Several secondary outcome assessments in the two studies showed statistically significant improvements with rasagiline. These included effects on the activities of daily living (ADL) subscale of the UPDRS performed during an “OFF” period and the motor subscale of the UPDRS performed during an “ON” period. In both scales, a negative response represents improvement. Tables 9 and 10 show these results for Studies 3 and 4.

Table 9: Secondary Measures of Effectiveness in Study 3
 | Baseline (score) | Change from baseline to last value
UPDRS ADL (Activities of Daily Living) subscale score while “OFF”
Placebo | 15.5 | 0.68
AZILECT 0.5 mg | 15.8 | -0.60
AZILECT 1 mg | 15.5 | -0.68
UPDRS Motor subscale score while “ON”
Placebo | 20.8 | 1.21
AZILECT 0.5 mg | 21.5 | -1.43
AZILECT 1 mg | 20.9 | -1.30

Table 10: Secondary Measures of Effectiveness in Study 4
 | Baseline (score) | Change from baseline to last value
UPDRS ADL (Activities of Daily Living) subscale score while “OFF”
Placebo | 18.7 | -0.89
AZILECT 1 mg | 19.0 | -2.61
UPDRS Motor subscale score while “ON”
Placebo | 23.5 | -0.82
AZILECT 1 mg | 23.8 | -3.87

16 HOW SUPPLIED/STORAGE AND HANDLING

AZILECT 0.5 mg Tablets:

White to off-white, round, flat, beveled tablets, debossed with “GIL 0.5” on one side and plain on the other side. Supplied as bottles of 30 tablets (NDC 68546-142-56).

AZILECT 1 mg Tablets:

White to off-white, round, flat, beveled tablets, debossed with “GIL 1” on one side and plain on the other side. Supplied as bottles of 30 tablets (NDC 68546-229-56).

Storage:

Store at 25°C (77°F) with excursions permitted to 15°-30°C (59°-86°F).

17 PATIENT COUNSELING INFORMATION

Hypertension

Advise patients that treatment with recommended doses of AZILECT may be associated with elevations of blood pressure. Tell patients who experience elevation of blood pressure while taking AZILECT to contact their healthcare provider.

The risk of using higher than recommended daily doses of AZILECT should be explained, and a brief description of the tyramine associated hypertensive reaction provided.

Advise patients to avoid certain foods (e.g., aged cheese) containing a very large amount of tyramine while taking recommended doses of AZILECT because of the potential for large increases in blood pressure. If patients eat foods very rich in tyramine and do not feel well soon after eating, they should contact their healthcare provider [see Warnings and Precautions (5.1)].

Serotonin Syndrome

Tell patients to inform their physician if they are taking, or planning to take, any prescription or over-the-counter drugs, especially antidepressants and over-the-counter cold medications, since there is a potential for interaction with AZILECT. Because patients should not use meperidine or certain other analgesics with AZILECT, they should contact their healthcare provider before taking analgesics [see Contraindications (4) and Warnings and Precautions (5.2)].

Falling Asleep During Activities of Daily Living and Somnolence

Advise and alert patients about the potential for sedating effects associated with AZILECT and other dopaminergic medications, including somnolence and particularly to the possibility of falling asleep while engaged in activities of daily living. Because somnolence can be a frequent adverse reaction with potentially serious consequences, patients should neither drive a car nor engage in other potentially dangerous activities until they have gained sufficient experience with AZILECT and other dopaminergic medications to gauge whether or not it affects their mental and/or motor performance adversely. Advise patients that if increased somnolence or new episodes of falling asleep during activities of daily living (e.g., watching television, passenger in a car, etc.) are experienced at any time during treatment, they should not drive or participate in potentially dangerous activities until they have contacted their physician. Patients should not drive, operate machinery, or work at heights during treatment if they have previously experienced somnolence and/or have fallen asleep without warning prior to use of AZILECT.

Because of possible additive effects, advise patients to exercise caution when patients are taking other sedating medications, alcohol, or other central nervous system depressants (e.g., benzodiazepines, antipsychotics, antidepressants) in combination with AZILECT or when taking concomitant medications that increase plasma levels of rasagiline (e.g., ciprofloxacin) [see Warnings and Precautions (5.3)].

Ciprofloxacin or Other CYP1A2 Inhibitors

Inform patients that they should contact their healthcare provider of AZILECT if they take ciprofloxacin or a similar drug that could increase blood levels of rasagiline because of the need to adjust the dose of AZILECT [see Dosage and Administration (2.2) and Warnings and Precautions (5.4)].

Hepatic Impairment

Tell patients who have hepatic problems to contact their healthcare provider regarding possible changes in AZILECT dosing [see Warnings and Precautions (5.5)].

Hypotension / Orthostatic Hypotension

Patients should be advised that they may develop orthostatic hypotension with or without symptoms such as dizziness, nausea, syncope, and sometimes sweating. Hypotension and/or orthostatic symptoms may occur more frequently during initial therapy or with an increase in dose at any time (cases have been seen after weeks of treatment). Accordingly, patients should be cautioned against standing up rapidly after sitting or lying down, especially if they have been doing so for prolonged periods, and especially, at the initiation of treatment with AZILECT [see Warnings and Precautions (5.6)].

Dyskinesia

Advise patients taking AZILECT as adjunct to levodopa that there is a possibility of dyskinesia or increased dyskinesia [see Warnings and Precautions (5.7)].

Hallucinations / Psychotic-Like Behavior

Inform patients that hallucinations or other manifestations of psychotic-like behavior can occur when taking AZILECT. Advise patients that, if they have a major psychotic disorder, that AZILECT should not ordinarily be used because of the risk of exacerbating the psychosis. Patients with a major psychotic disorder should also be aware that many treatments for psychosis may decrease the effectiveness of AZILECT [see Warnings and Precautions (5.8)].

Impulse Control/Compulsive Behaviors

Advise patients that they may experience intense urges to gamble, increased sexual urges, other intense urges, and the inability to control these urges while taking one or more of the medications that increase central dopaminergic tone and that are generally used for the treatment of Parkinson’s disease (including AZILECT). Although it is not proven that the medications caused these events, these urges were reported to have stopped in some cases when the dose was reduced or the medication was stopped. Prescribers should ask patients about the development of new or increased gambling urges, sexual urges, or other urges while being treated with AZILECT. Patients should inform their physician if they experience new or increased gambling urges, increased sexual urges, or other intense urges while taking AZILECT. Physicians should consider dose reduction or stopping the medication if a patient develops such urges while taking AZILECT [see Warnings and Precautions (5.9)].

Withdrawal-Emergent Hyperpyrexia and Confusion

Tell patients to contact their healthcare provider if they wish to discontinue AZILECT [see Warnings and Precautions (5.10)].

Missing Dose

Instruct patients to take AZILECT as prescribed. If a dose is missed, the patient should not double-up the dose of AZILECT. The next dose should be taken at the usual time on the following day.

Pregnancy

Advise patients to notify their healthcare provider if they are pregnant or plan to become pregnant [see Use in Specific Populations (8.1)].

AZI-004

Distributed by: Teva Pharmaceuticals USA, Inc., Parsippany, NJ 07054

©2020 Teva Neuroscience, Inc.

Package/Label Display Panel

NDC 68546-142-56
AZILECT® (rasagiline tablets)
0.5 mg
30 Tablets Rx only

Package/Label Display Panel

NDC 68546-229-56
AZILECT® (rasagiline tablets)
1 mg
30 Tablets Rx only